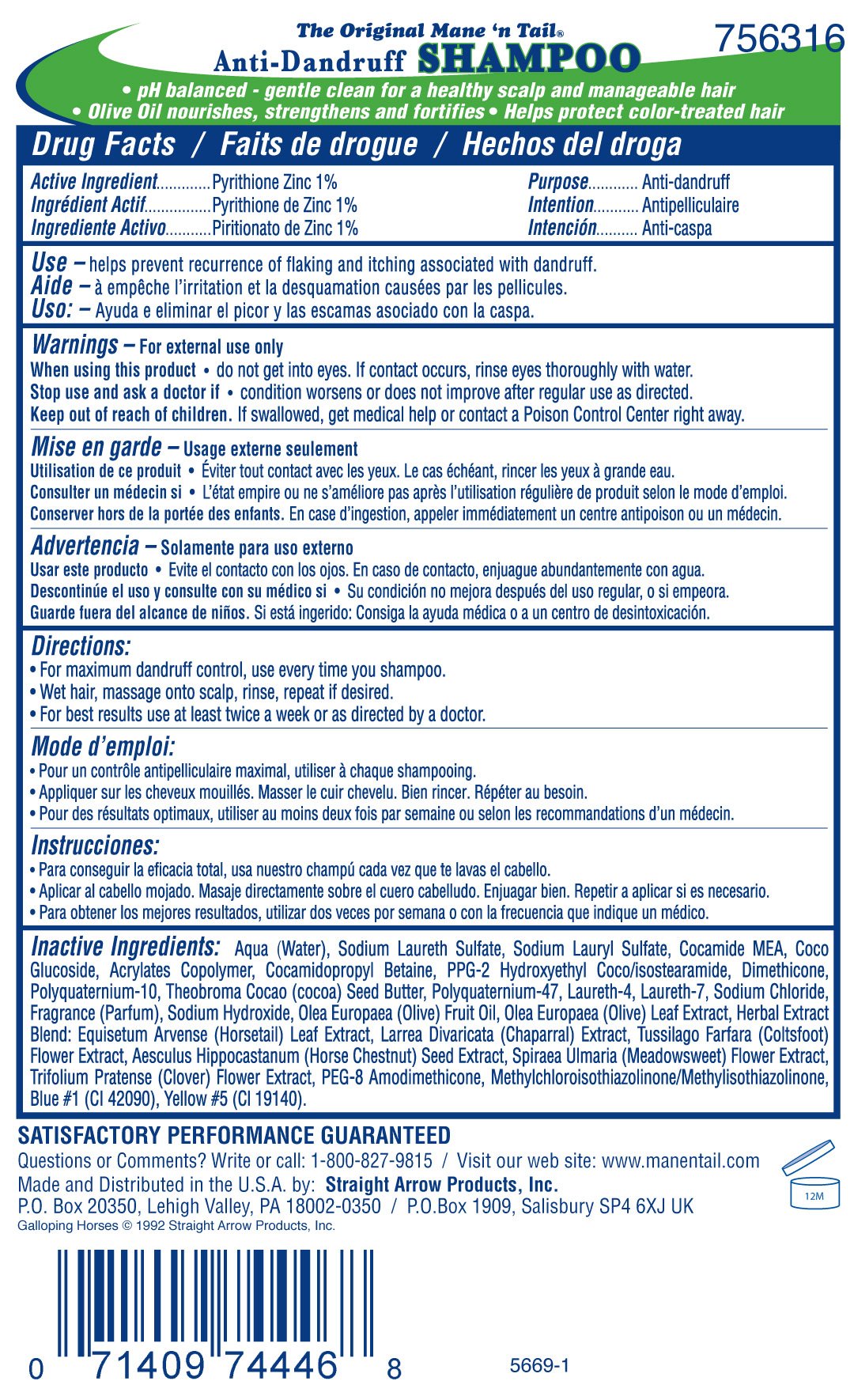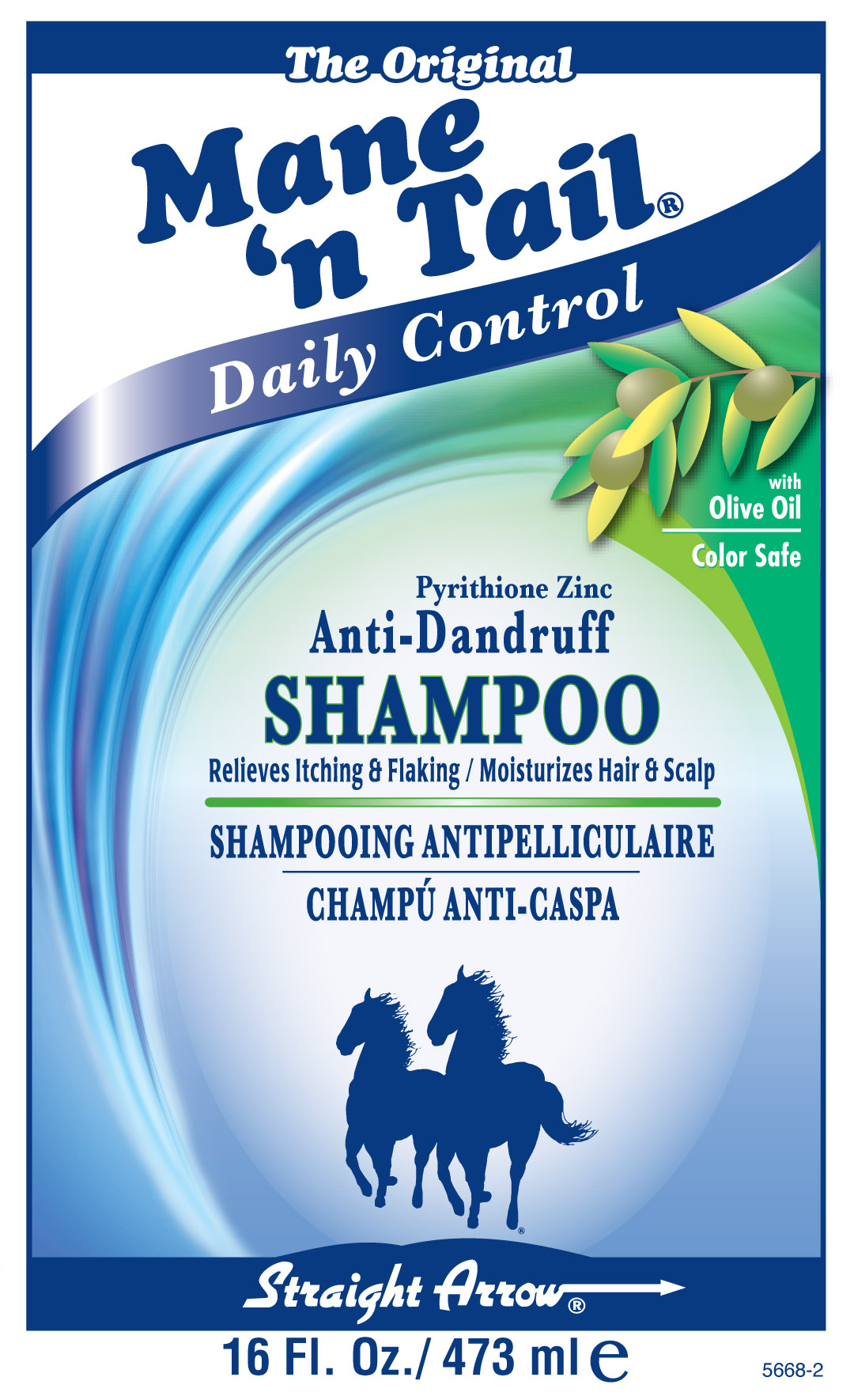 DRUG LABEL: Mane n Tail Daily Control Anti-Dandruff
NDC: 62001-0319 | Form: SHAMPOO, SUSPENSION
Manufacturer: Straight Arrow Products, Inc.
Category: otc | Type: HUMAN OTC DRUG LABEL
Date: 20101005

ACTIVE INGREDIENTS: PYRITHIONE ZINC .01 g/1 g
INACTIVE INGREDIENTS: WATER; SODIUM LAURETH SULFATE; SODIUM LAURYL SULFATE; COCO MONOETHANOLAMIDE; COCAMIDOPROPYL BETAINE; DIMETHICONE; COCOA BUTTER; LAURETH-4; LAURETH-7; SODIUM CHLORIDE; CITRIC ACID; SODIUM HYDROXIDE; ALMOND OIL; OLIVE OIL; EQUISETUM ARVENSE TOP; LARREA TRIDENTATA TOP; TUSSILAGO FARFARA; HORSE CHESTNUT; FILIPENDULA ULMARIA FLOWER; RED CLOVER; METHYLCHLOROISOTHIAZOLINONE; METHYLISOTHIAZOLINONE; FD&C BLUE NO. 1; FD&C YELLOW NO. 5

Active Ingredient
Pyrithione Zinc 1%

Purpose
Anti-dandruff

INDICATIONS AND USAGE

Use -helps prevent recurrence of flaking and itching associated with dandruff.

Warnings - For external use only

When using this product

- do not get into eyes. If contact occurs, rinse eyes thoroughly with water.

Stop use and ask a doctor if

- if condition worsens or does not improve after regular use as directed.

Keep out of reach of children. If swallowed, get medical help or contact a Poison Control Center right away.

Directions:

- For maximum dandruff control, use every time you shampoo.
- Wet hair, massage onto scalp, rinse, repeat if desired.
- For best results, use at least twice a week or as directed by a doctor.

INACTIVE INGREDIENT

Inactive Ingredients: Aqua (Water), Sodium Laureth Sulfate, Sodium Lauryl Sulfate, Cocamide MEA, Coco Glucoside, Acrylates Copolymer, Cocamidopropyl Betaine, Fragrance (Parfum), Sodium Hydroxide, Olea Europaea (Olive) Fruit Oil, Olea Europaea (Olive) Leaf Extract, Herbal Extract Blend: Equisetum Arvense (Horsetail) Leaf Extract, Larrea Divaricata (Chaparral) Extract, Tussilago Farfara (Coltsfoot) Flower Extract, Aesculus Hippocastanum (Horse Chestnut) Seed Extract, Spiraea Ulmaria (Meadowsweet) Flower Extract, Trifolium Pratense (Clover) Flower Extract, PEG-8 Amodimethicone, Methylchloroisothiazolinone/Methylisothiazolinone, Blue #1 (CI 42090), Yellow #5 (CI 19140).